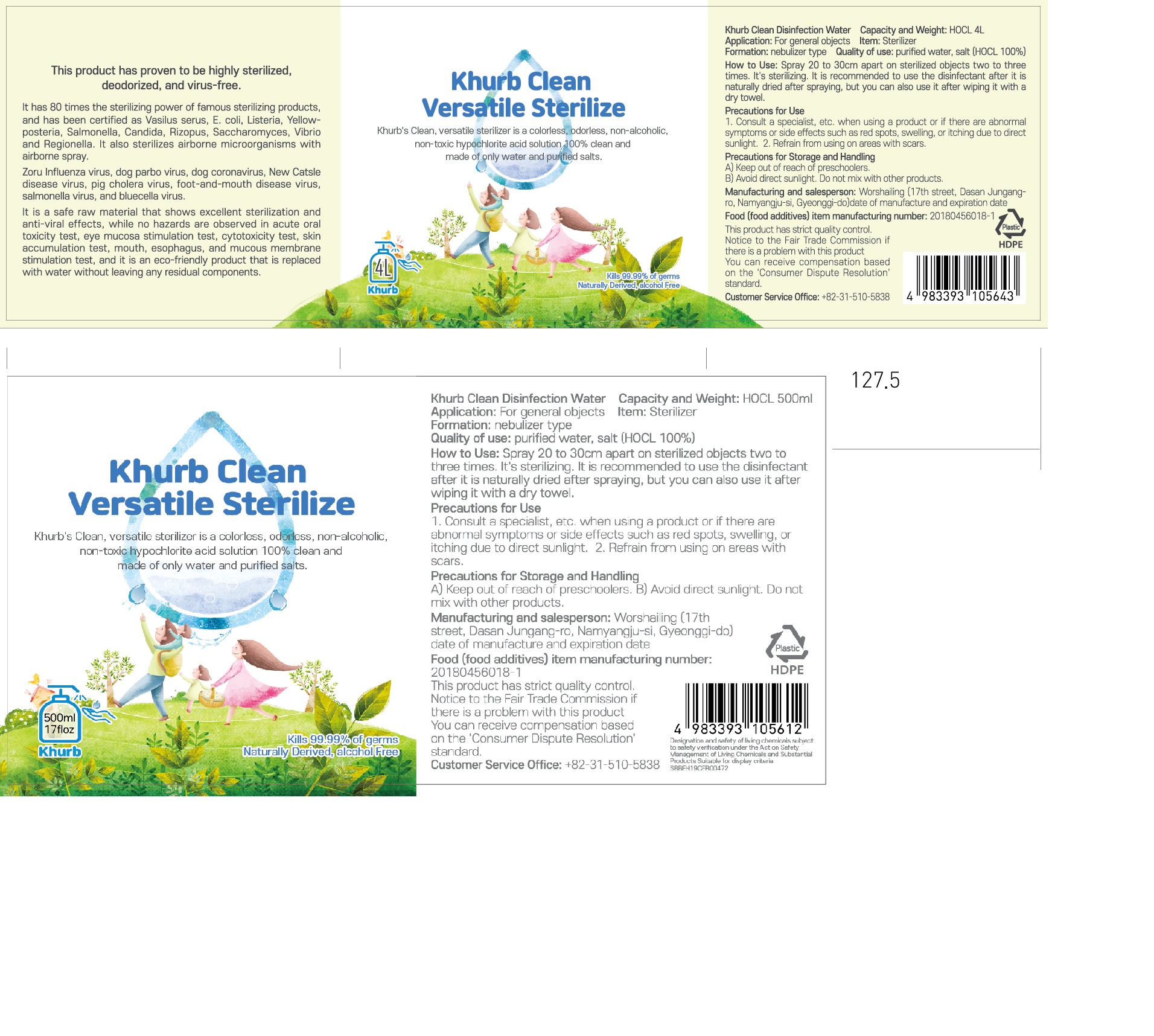 DRUG LABEL: Khurb clean disinfection water
NDC: 76862-0001 | Form: LIQUID
Manufacturer: WorthBuying
Category: otc | Type: HUMAN OTC DRUG LABEL
Date: 20200429

ACTIVE INGREDIENTS: HYPOCHLOROUS ACID 100 g/100 mL
INACTIVE INGREDIENTS: WATER

Drug Facts

ACTIVE INGREDIENT

HOCL

INACTIVE INGREDIENT

n/a

KEEP OUT OF REACH OF THE CHILDREN

PURPOSE

hand sanitizer to help reduce bacteria that potentially can cause disease

for use when soap and water are not available

INDICATIONS AND USAGE

Spray 20 to 30cm apart on sterilized objects two to three times.
It's sterilizing. It is recommended to use the disinfectant after it is naturally dried after spraying, but you can also use it after wiping it with a dry towel.

WARNINGS

For external use only.

Flammable, keep away from fire or flame.

When using this product keep out of eyes. If contact with eyes occurs, rinse promptly and thoroughly with water.

Stop use and ask a doctor if significant irritation or sensitization develops.

Keep out of reach of children. If swallowed, get medical help or contact a Poison Control Center right away.

DOSAGE AND ADMINISTRATION

for external use only